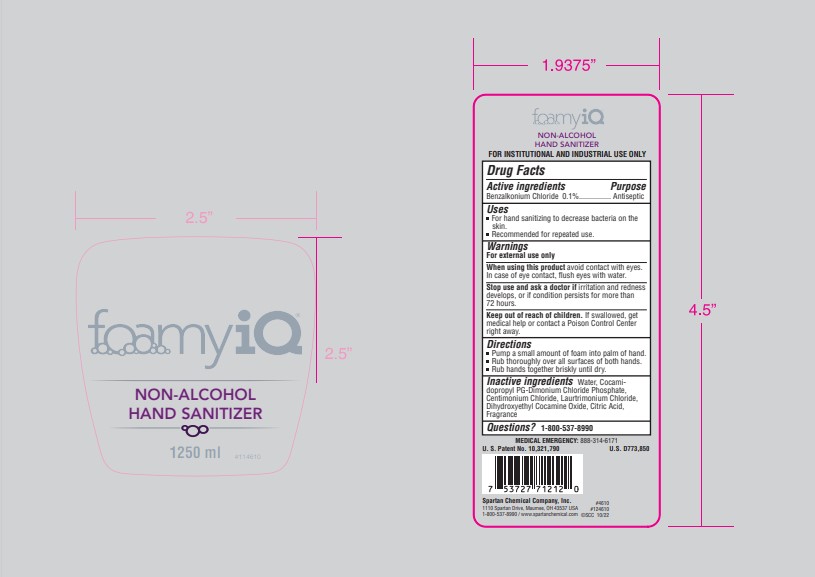 DRUG LABEL: FoamyiQ Non-Alcohol Hand Sanitizer
NDC: 64009-221 | Form: SOAP
Manufacturer: Spartan Chemical Company
Category: otc | Type: HUMAN OTC DRUG LABEL
Date: 20231219

ACTIVE INGREDIENTS: BENZALKONIUM CHLORIDE 1 g/1000 g
INACTIVE INGREDIENTS: DIHYDROXYETHYL COCAMINE OXIDE; WATER; COCAMIDOPROPYL PG-DIMONIUM CHLORIDE PHOSPHATE; CETRIMONIUM CHLORIDE; FRAGRANCE 13576; CITRIC ACID MONOHYDRATE; LAURTRIMONIUM CHLORIDE

Active Ingredients

Benzalkonium chloride 0.1%

Purpose

antiseptic

Uses

For hand sanitizing to decrease bacteria on the skin

Recommended for repeated use

Warnings

For external use only

when using this product avoid contact with eyes. in case of eye contact, flush eyes with water

stop use and ask a doctor if irritation and redness develops, or if condition persists for more than 72 hours

keep out of reach of children. if swallowed, get medical help or contact a poison control center right away

Warnings

Keep out of reach of children. If swallowed, get medical help or contact a poison control center right away

Directions

pump a small amount of foam into palm of hand

rub thoroughly over all surfaces of both hands

rub hands together briskly until dry

Inactive Ingredients

Water, Cocomidopropyl PG-Dimonium Chloride Phosphate, Centimonium Chloride, Lautrimonium Chloride, Dihydroxyethyl cocamide oxide, citric acid, fragrance

Questions?

1-800-537-8990